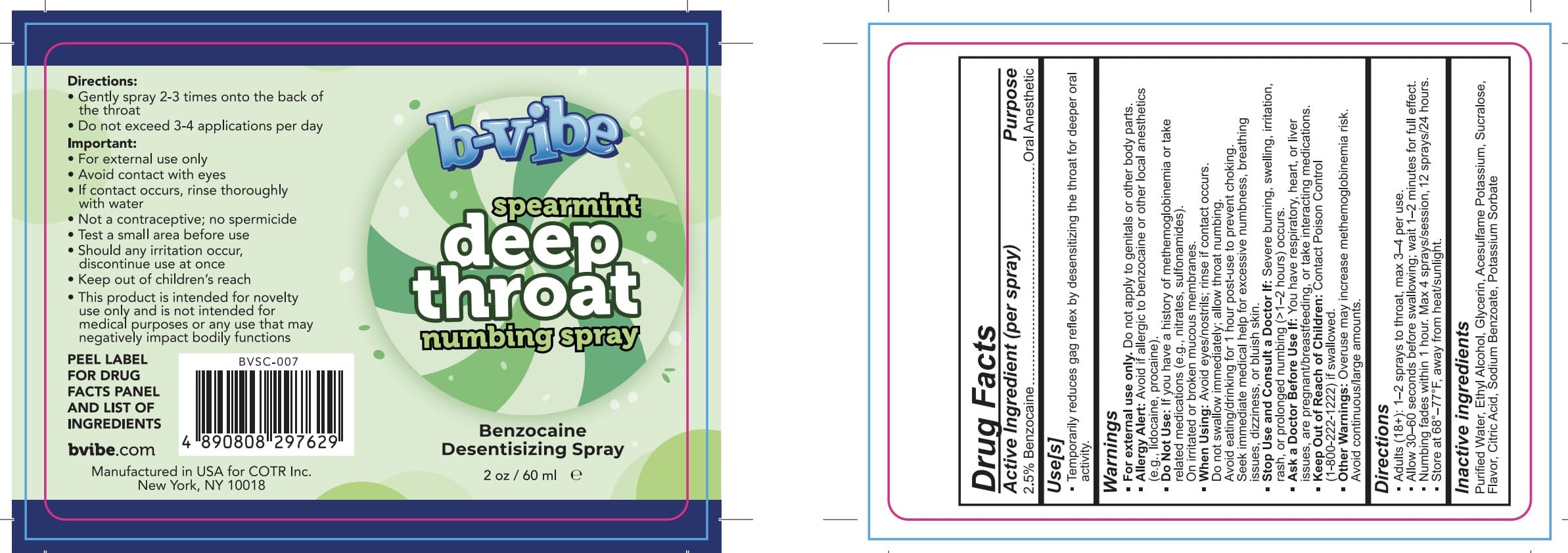 DRUG LABEL: BVibe Spearmint Deep Throat
NDC: 85775-112 | Form: LIQUID
Manufacturer: COTR Inc
Category: otc | Type: HUMAN OTC DRUG LABEL
Date: 20250822

ACTIVE INGREDIENTS: BENZOCAINE 25 mg/1 mL
INACTIVE INGREDIENTS: ACESULFAME POTASSIUM; SUCRALOSE; ALCOHOL; WATER; CITRIC ACID; SODIUM BENZOATE; SPEARMINT; POTASSIUM SORBATE; GLYCERIN

COTR-PLP Deep Throat

Active Ingredient(s)

Benzocaine 2.5%

Purpose

Oral Anesthetic

Use

Temporarily reduces gag reflex by desensitizing the throat for deeper oral activity.

Warnings

For external use only. Do not apply to genitals or other body parts.
Allergy Alert: Avoid if allergic to benzocaine or other local anesthetics (e.g., lidocaine, procaine)
Do Not Use: If you have a history of methemoglobinemia or take related medications (e.g., nitrates, sulfonamides).
On irritated or broken mucous membranes.
When Using: Avoid eyes/nostrils; rinse if contact occurs.
Do not swallow immediately; allow throat numbing.
Avoid eating/drinking for 1 hour post-use to prevent choking.
Seek immediate medical help for excessive numbness, breathing issues, dizziness, or bluish skin.

Stop Use and Consult a Doctor If: Severe burning, swelling, irritation, rash, or prolonged numbing (>1-2 hours) occurs.

Ask a Doctor Before Use If: You have respiratory, heart, or liver issues, are pregnant/breastfeeding, or take interacting medications.

Keep Out of Reach of Children: Contact Poison Control

(1-800-222-1222) if swallowed.

• Other Warnings: Overuse may increase methemoglobinemia risk.
Avoid continuous/large

KEEP OUT OF REACH OF CHILDREN

Keep out of reach of childeren.Contact Poison Control if

Directions

Adults (18+): 1-2 sprays to throat, max 3-4 per use.
Allow 30-60 seconds before swallowing; wait 1-2 minutes for full effect.
Numbing fades within 1 hour. Max 4 sprays/session, 12 sprays/24 hours.

Store at 68°-77°F, away from heat/sunlight.

Inactive ingredients

Purified Water, Ethyl Alcohol, Glycerin, Acesulfame Potassium, Sucralose, Flavor, Citric Acid, Sodium Benzoate, Potassium